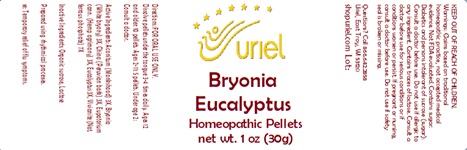 DRUG LABEL: Bryonia Eucalyptus
NDC: 48951-2136 | Form: PELLET
Manufacturer: Uriel Pharmacy Inc.
Category: homeopathic | Type: HUMAN OTC DRUG LABEL
Date: 20241204

ACTIVE INGREDIENTS: ACONITUM NAPELLUS 3 [hp_X]/1 1; EUPATORIUM PERFOLIATUM FLOWERING TOP 3 [hp_X]/1 1; FERROSOFERRIC PHOSPHATE 7 [hp_X]/1 1; BRYONIA ALBA ROOT 3 [hp_X]/1 1; EUCALYPTUS GUM 3 [hp_X]/1 1; QUILLAJA SAPONARIA BARK 3 [hp_X]/1 1
INACTIVE INGREDIENTS: SUCROSE; LACTOSE, UNSPECIFIED FORM

Bryonia Eucalyptus

INDICATIONS AND USAGE

Directions: FOR ORAL USE ONLY.

DOSAGE AND ADMINISTRATION

Dissolve pellets under the tongue 3-4 times daily. Ages 12 and older: 10 pellets. Ages 2-11: 5 pellets. Under age 2: Consult a doctor.

ACTIVE INGREDIENT

Active Ingredients: Aconitum (Monkshood) 3X, Bryonia (White bryony) 3X, China (Peruvian bark) 3X, Eupatorium cann. (Hemp agrimony) 3X, Eucalyptus 3X, Vivianite (Nat. ferrous phosphate) 7X

Inactive Ingredients: Organic sucrose, Lactose

PURPOSE

Use: Temporary relief of flu symptoms.

KEEP OUT OF REACH OF CHILDREN.

WARNINGS

Warnings: Claims based on traditional homeopathic practice, not accepted medical evidence. Not FDA evaluated. Contains sugar. Diabetics and persons intolerant of sucrose (sugar): Consult a doctor before use. Do not use if allergic to any ingredient. Contains traces of lactose. Consult a doctor before use for serious conditions or if conditions worsen or persist. If pregnant or nursing, consult a doctor before use. Do not use if safety seal is broken or missing.

Questions? Call 866.642.2858
Uriel, East Troy, WI 53120
shopuriel.com Lot: